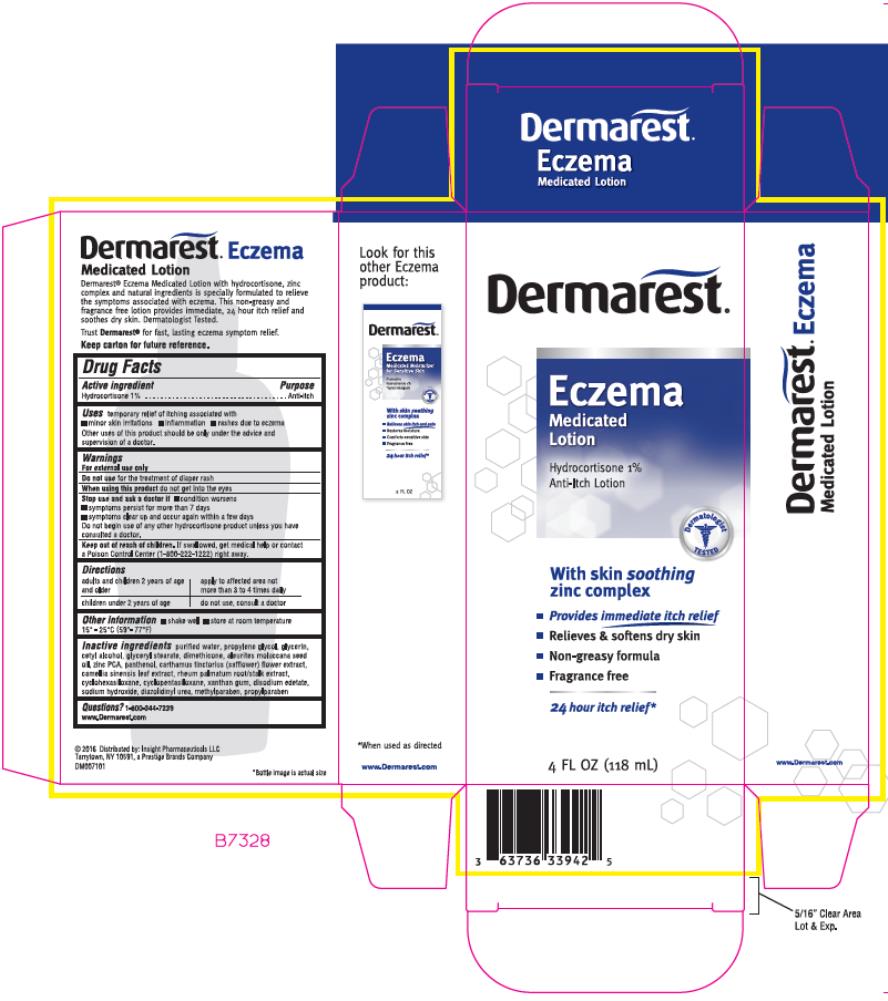 DRUG LABEL: Dermarest
NDC: 63736-339 | Form: LOTION
Manufacturer: Insight Pharmaceuticals LLC
Category: otc | Type: HUMAN OTC DRUG LABEL
Date: 20241025

ACTIVE INGREDIENTS: HYDROCORTISONE 10 mg/1 mL
INACTIVE INGREDIENTS: WATER; PROPYLENE GLYCOL; GLYCERIN; CETYL ALCOHOL; GLYCERYL MONOSTEARATE; DIMETHICONE; KUKUI NUT OIL; ZINC PIDOLATE; PANTHENOL; SAFFLOWER; GREEN TEA LEAF; RHEUM PALMATUM ROOT; CYCLOMETHICONE 6; CYCLOMETHICONE 5; XANTHAN GUM; EDETATE DISODIUM; SODIUM HYDROXIDE; DIAZOLIDINYL UREA; METHYLPARABEN; PROPYLPARABEN

Dermarest Eczema Medicated Lotion

Dermarest™ Eczema
Medicated Lotion

Keep carton for future reference.

Drug Facts

Active ingredient

Hydrocortisone 1%

Purpose

Anti-itch

Uses

temporary relief of itching associated with

- minor skin irritations
- inflammation
- rashes due to eczema

Other uses of this product should be only under the advice and supervision of a doctor.

Warnings

For external use only

Do not use

for the treatment of diaper rash

When using this product

do not get into the eyes.

Stop use and ask a doctor if

- condition worsens
- symptoms persist for more than 7 days
- symptoms clear up and occur again within a few days

Do not begin use of any other hydrocortisone product unless you have consulted a doctor.

Keep out of reach of children.

If swallowed, get medical help or contact a Poison Control Center (1-800-222-1222) right away.

Directions

adults and children 2 years of age and older | apply to affected area not more than 3 to 4 times daily
children under 2 years of age | do not use, consult a doctor

Other Information

- shake well
- store at room temperature 15° - 25°C (59°- 77°F)

Inactive ingredients

Purified water, propylene glycol, glycerin, cetyl alcohol, glyceryl stearate, dimethicone, aleurites moluccana seed oil, zinc PCA, panthenol, carthamus tinctorius (safflower) flower extract, camellia sinensis leaf extract, rheum palmatum root/stalk extract, cyclohexasiloxane, cyclopentasiloxane, xanthan gum, disodium edetate, sodium hydroxide, diazolidinyl urea, methylparaben, propylparaben

Questions?

1-800-344-7239 www.Dermarest.com

PRINCIPAL DISPLAY PANEL

Dermarest®
Eczema
Medicated
Lotion
Hydrocortisone 1%
Anti-Itch Lotion
4 FL OZ (118 mL)